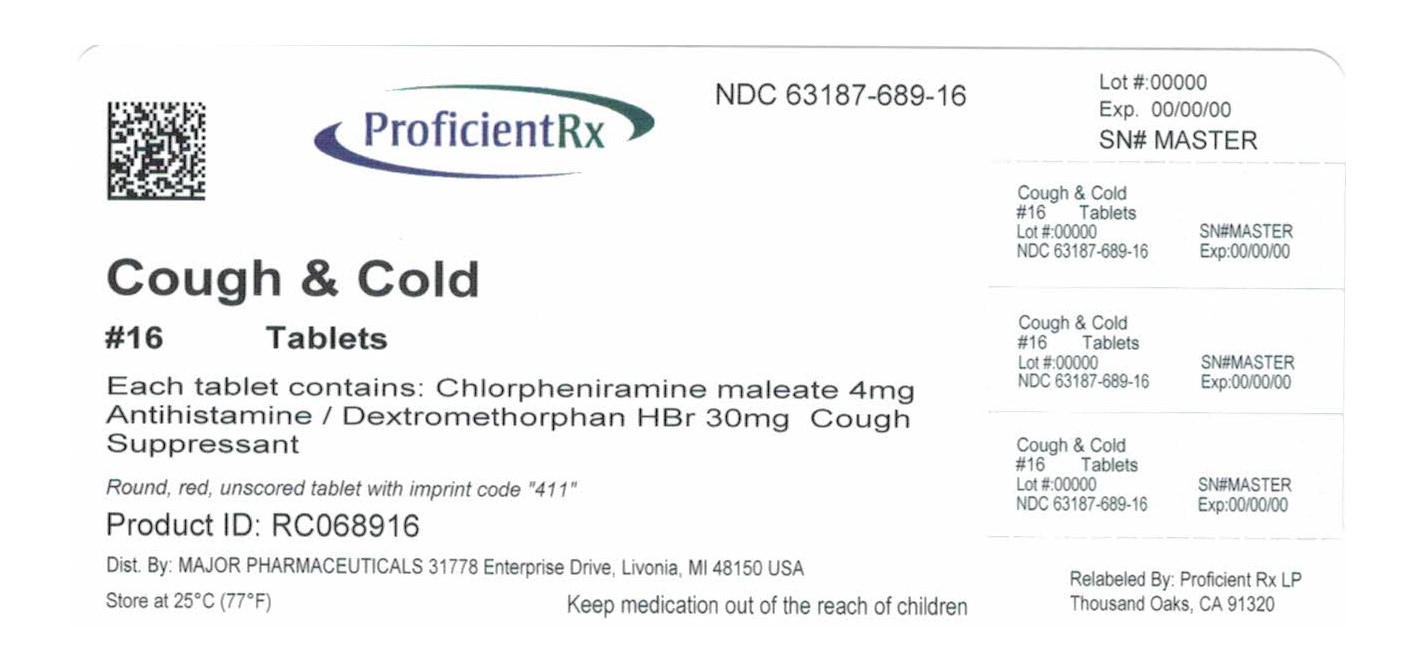 DRUG LABEL: Cough and Cold
NDC: 63187-689 | Form: TABLET, SUGAR COATED
Manufacturer: Proficient Rx LP
Category: otc | Type: HUMAN OTC DRUG LABEL
Date: 20181201

ACTIVE INGREDIENTS: CHLORPHENIRAMINE MALEATE 4 mg/1 1; DEXTROMETHORPHAN HYDROBROMIDE 30 mg/1 1
INACTIVE INGREDIENTS: ACACIA; CALCIUM CARBONATE; CARNAUBA WAX; CROSCARMELLOSE SODIUM; D&C RED NO. 27; MAGNESIUM STEARATE; METHYLPARABEN; MICROCRYSTALLINE CELLULOSE; POVIDONE, UNSPECIFIED; PROPYLPARABEN; PROPYLENE GLYCOL; SHELLAC; SODIUM BENZOATE; STEARIC ACID; TALC; TITANIUM DIOXIDE

Major 44-411

Active ingredients (in each tablet)

Chlorpheniramine maleate 4 mg
Dextromethorphan HBr 30 mg

Purpose

Antihistamine
Cough suppressant

Uses

- temporarily relieves cough due to minor throat and bronchial irritation as may occur with a cold
- temporarily relieves runny nose and sneezing due to the common cold

Warnings

Do not use

if you are now taking a prescription monoamine oxidase inhibitor (MAOI) (certain drugs for depression, psychiatric or emotional conditions, or Parkinson's disease), or for 2 weeks after stopping the MAOI drug. If you do not know if your prescription drug contains an MAOI, ask a doctor or pharmacist before taking this product.

Ask a doctor before use if you have

- trouble urinating due to an enlarged prostate gland
- glaucoma
- cough that occurs with excessive phlegm (mucus)
- a breathing problem or persistent or chronic cough as occurs with smoking, asthma, chronic bronchitis, or emphysema

Ask a doctor or pharmacist before use if you are

taking sedatives or tranquilizers.

When using this product

- excitability may occur, especially in children
- marked drowsiness may occur
- avoid alcoholic beverages
- alcohol, sedatives, and tranquilizers may increase drowsiness
- use caution when driving a motor vehicle or operating machinery

Stop use and ask a doctor if

persistent cough lasts for more than one week, tends to recur, or is accompanied by fever, rash, or persistent headache. These could be signs of a serious condition.

If pregnant or breast-feeding,

ask a health professional before use.

Keep out of reach of children.

In case of overdose, get medical help or contact a Poison Control Center (1-800-222-1222) right away.

Directions

- do not exceed recommended dose
- adults and children 12 years and over: 1 tablet every 6 hours. Do not take more than 4 tablets in 24 hours
- children under 12 years: do not use

Other information

- TAMPER EVIDENT: DO NOT USE IF OUTER PACKAGE IS OPENED OR BLISTER IS TORN OR BROKEN
- store at 25ºC (77ºF); excursions permitted between 15º-30ºC (59º-86ºF)
- see end flap for expiration date and lot number

Inactive ingredients

acacia, black iron oxide, calcium carbonate, carnauba was, croscarmellose sodium, D&C red #27 aluminum lake, FD&C yellow #6 aluminum lake, lactose, magnesium stearate, methylparaben, microcrystalline cellulose, povidone, propylparaben, propylene glycol, shellac, silica gel, sodium benzoate, stearic acid, sugar, talc, titanium dioxide

Questions or comments?

(800) 616-2471

Principal Display Panel

MAJOR®

NDC 63187-689-16

*Compare to the active ingredients in Coricidin® HBP Cough & Cold

Cough & Cold
Relief for people with High Blood Pressure
Chlorpheniramine maleate - Antihistamine
Dextromethorphan HBr - Cough Suppressant

Decongestant Free

Relieves
• Cough • Runny Nose • Sneezing

16 TABLETS

TAMPER EVIDENT: DO NOT USE IF PACKAGE IS OPENED OR IF BLISTER UNIT IS TORN, BROKEN OR SHOWS ANY SIGNS OF TAMPERING

*This product is not manufactured or distributed by MSD Consumer Care, Inc., owner of the registered trademark Coricidin® HBP Cough & Cold.
50844 REV0714D41121

Distributed by MAJOR® PHARMACEUTICALS
31778 Enterprise Drive, Livonia, MI 48150 USA M-17
Re-order No. 873602 Rev. 08/14

Relabeled By: Proficient Rx LP

Thousand Oaks, CA 91320

Major 44-411